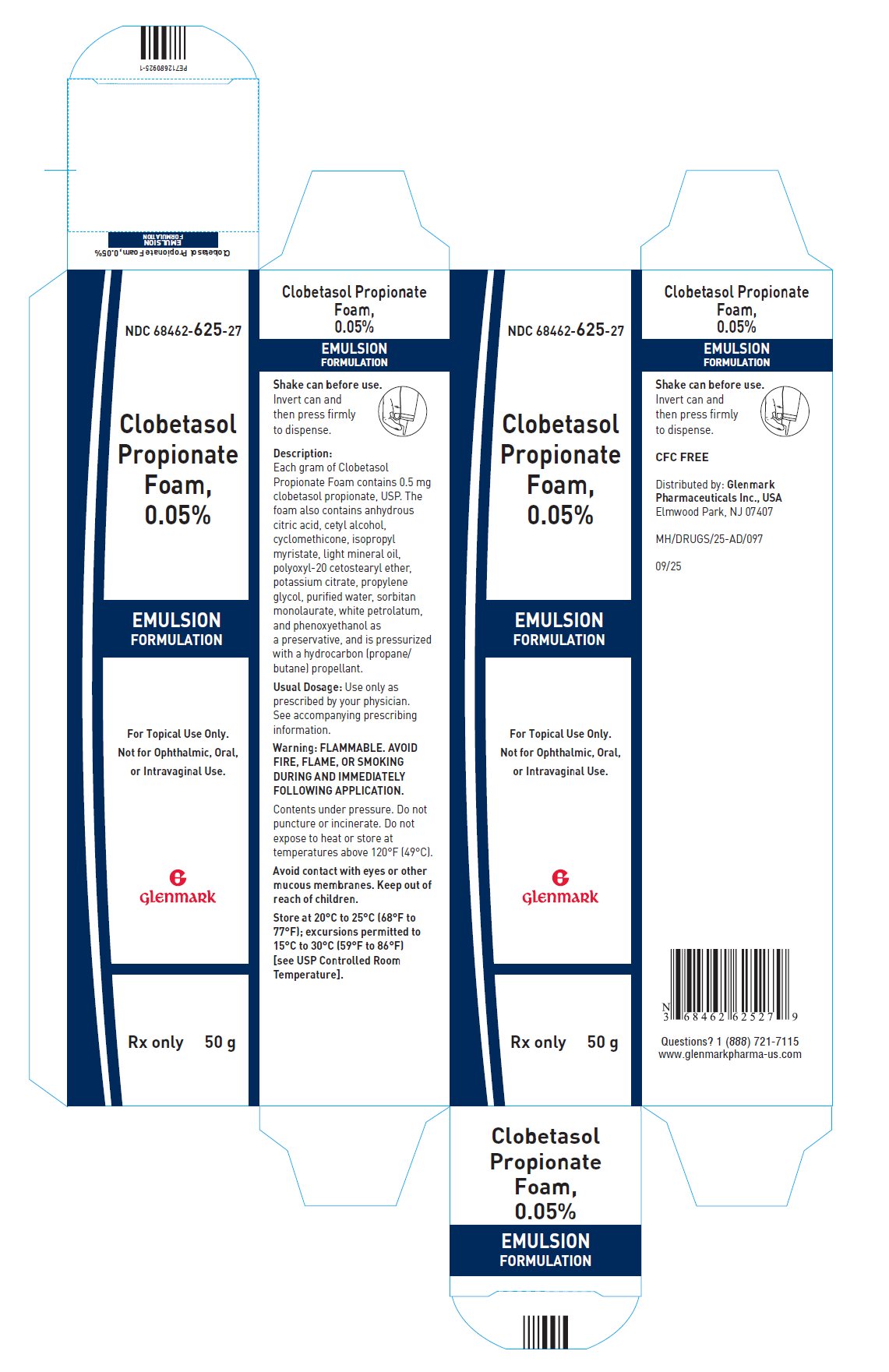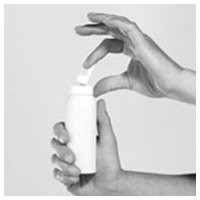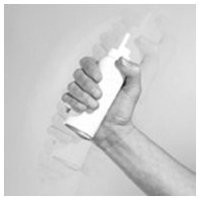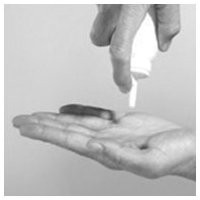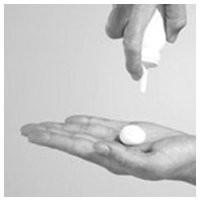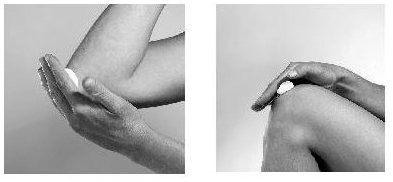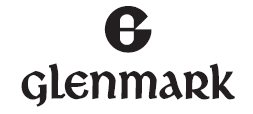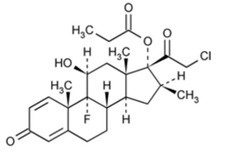 DRUG LABEL: clobetasol propionate
NDC: 68462-625 | Form: AEROSOL, FOAM
Manufacturer: Glenmark Pharmaceuticals Inc., USA
Category: prescription | Type: HUMAN PRESCRIPTION DRUG LABEL
Date: 20260131

ACTIVE INGREDIENTS: CLOBETASOL PROPIONATE 0.5 mg/1 g
INACTIVE INGREDIENTS: ANHYDROUS CITRIC ACID; CETYL ALCOHOL; CYCLOMETHICONE; ISOPROPYL MYRISTATE; LIGHT MINERAL OIL; POLYOXYL 20 CETOSTEARYL ETHER; POTASSIUM CITRATE; PROPYLENE GLYCOL; WATER; SORBITAN MONOLAURATE; PETROLATUM; PHENOXYETHANOL; PROPANE; BUTANE

HIGHLIGHTS OF PRESCRIBING INFORMATION

These highlights do not include all the information needed to use CLOBETASOL PROPIONATE FOAM safely and effectively. See full prescribing information for CLOBETASOL PROPIONATE FOAM.
CLOBETASOL PROPIONATE foam, for topical use
Initial U.S. Approval: 1985

1 INDICATIONS AND USAGE

Clobetasol propionate emulsion foam is a corticosteroid indicated for the treatment of inflammatory and pruritic manifestations of corticosteroid-responsive dermatoses in patients aged 12 years and older. (1)

2 DOSAGE AND ADMINISTRATION

Clobetasol propionate emulsion foam is not for oral, ophthalmic, or intravaginal use. (2)

- Apply clobetasol propionate emulsion foam to the affected area(s) twice daily, morning and evening, for up to 2 consecutive weeks. The maximum weekly dose should not exceed 50 g. (2)
- Avoid use on face, axilla, and groin, or if skin atrophy is present at the treatment site. (2)

3 DOSAGE FORMS AND STRENGTHS

Foam, 0.05%. (3)

4 CONTRAINDICATIONS

None. (4)

5 WARNINGS AND PRECAUTIONS

- Clobetasol propionate emulsion foam has been shown to suppress the HPA axis. Systemic absorption of clobetasol propionate emulsion foam may produce reversible HPA axis suppression, Cushing’s syndrome, hyperglycemia, and unmask latent diabetes. (5.1)
- Because of the potential for systemic absorption, use of topical corticosteroids may require that patients be periodically evaluated for HPA axis suppression. (5.1)
- Modify use should HPA axis suppression develop. (5.1)
- High potency corticosteroids, large treatment surface areas, prolonged use, use of occlusive dressings, altered skin barrier, and liver failure may predispose patients to HPA axis suppression. (5.1)
- May increase the risk of cataract and glaucoma. If visual symptoms occur, consider referral to an ophthalmologist for evaluation. (5.3)
- Pediatric patients may be more susceptible to systemic toxicity when treated with topical corticosteroids. (5.1, 8.4)
- The propellant in clobetasol propionate emulsion foam is flammable. Avoid fire, flame, or smoking during and immediately following application. (5.5)

6 ADVERSE REACTIONS

- The most common adverse reactions (incidence ≥1%) are application site atrophy and application site reaction. (6.1)

To report SUSPECTED ADVERSE REACTIONS, contact Glenmark Pharmaceuticals Inc., USA at 1 (888) 721-7115 or FDA at 1-800-FDA-1088 or www.fda.gov/medwatch.

FULL PRESCRIBING INFORMATION

1 INDICATIONS AND USAGE

Clobetasol propionate emulsion foam is indicated for the treatment of inflammatory and pruritic manifestations of corticosteroid-responsive dermatoses in patients 12 years and older.

2 DOSAGE AND ADMINISTRATION

- Apply a thin layer of clobetasol propionate emulsion foam to the affected area(s) twice daily, morning and evening, for up to 2 consecutive weeks; therapy should be discontinued when control has been achieved.
- The maximum weekly dose should not exceed 50 g or an amount greater than 21 capfuls per week.
- For proper dispensing of foam, shake the can, hold it upside down, and depress the actuator.
- Dispense a small amount of foam (about a capful) and gently massage the medication into the affected areas (excluding the face, groin, and axillae) until the foam is absorbed.
- Clobetasol propionate emulsion foam is not for oral, ophthalmic, or intravaginal use.
- Avoid contact with the eyes.
- Avoid use on face, axillae, and groin, or if skin atrophy is present at the treatment site.
- Wash hands after each application.

3 DOSAGE FORMS AND STRENGTHS

Clobetasol Propionate Emulsion Foam, 0.05% contains 0.5 mg of clobetasol propionate, USP per gram in a white to off-white emulsion aerosol foam.

4 CONTRAINDICATIONS

None.

5 WARNINGS AND PRECAUTIONS

5.1 Effects on Endocrine System

Clobetasol propionate emulsion foam has been shown to suppress the hypothalamic-pituitary-adrenal (HPA) axis.

Systemic absorption of clobetasol propionate emulsion foam has caused reversible HPA axis suppression with the potential for clinical glucocorticoid insufficiency. This may occur during treatment or upon withdrawal of the topical corticosteroid. Use of clobetasol propionate emulsion foam for longer than 2 weeks may suppress the immune system [see Nonclinical Toxicology (13.1)].

In a trial including 37 subjects ages 12 years and older with atopic dermatitis of at least 30% body surface area (BSA), adrenal suppression was identified in 6 out of 37 subjects (16.2%) after 2 weeks of treatment with clobetasol propionate emulsion foam [see Clinical Pharmacology (12.2)].

Because of the potential for systemic absorption, use of clobetasol propionate emulsion foam may require that patients be periodically evaluated for HPA axis suppression. Factors that predispose a patient using a topical corticosteroid to HPA axis suppression include the use of more potent steroids, use over large surface areas, use over prolonged periods, use under occlusion, use on an altered skin barrier, and use in patients with liver failure.

An adrenocorticotrophic hormone (ACTH) stimulation test may be helpful in evaluating patients for HPA axis suppression. If HPA axis suppression is documented, an attempt should be made to gradually withdraw the drug, to reduce the frequency of application, or to substitute a less potent steroid. Manifestations of adrenal insufficiency may require systemic corticosteroids. Recovery of HPA axis function is generally prompt and complete upon discontinuation of topical corticosteroids.

Cushing’s syndrome, hyperglycemia, and unmasking of latent diabetes mellitus can also result from systemic absorption of topical corticosteroids.

Use of more than 1 corticosteroid-containing product at the same time may increase the total systemic corticosteroid exposure.

Pediatric patients may be more susceptible to systemic toxicity from equivalent doses because of their larger skin surface-to-body mass ratios [see Use in Specific Populations (8.4)].

5.2 Local Adverse Reactions with Topical Corticosteroids

Local adverse reactions may be more likely to occur with occlusive use, prolonged use, or use of higher potency corticosteroids. Reactions may include atrophy, striae, telangiectasias, burning, itching, irritation, dryness, folliculitis, acneiform eruptions, hypopigmentation, perioral dermatitis, allergic contact dermatitis, secondary infection, and miliaria. Some local adverse reactions may be irreversible.

Allergic contact dermatitis to any component of topical corticosteroids is usually diagnosed by a failure to heal rather than a clinical exacerbation. Clinical diagnosis of allergic contact dermatitis can be confirmed by patch testing.

If irritation develops, treatment with clobetasol propionate emulsion foam should be discontinued and appropriate therapy instituted.

5.3 Ophthalmic Adverse Reactions

Use of topical corticosteroids, including clobetasol propionate emulsion foam, may increase the risk of posterior subcapsular cataracts and glaucoma. Cataracts and glaucoma have been reported postmarketing with the use of topical corticosteroids, including topical clobetasol products [see Adverse Reactions (6.2)].

Avoid contact of clobetasol propionate emulsion foam with eyes. Advise patients to report any visual symptoms and consider referral to an ophthalmologist for evaluation.

5.4 Concomitant Skin Infections

Concomitant skin infections should be treated with an appropriate antimicrobial agent. If the infection persists, clobetasol propionate emulsion foam should be discontinued until the infection has been adequately treated.

5.5 Flammable Contents

The propellant in clobetasol propionate emulsion foam is flammable. Avoid fire, flame, or smoking during and immediately following application. Do not puncture and/or incinerate the containers. Do not expose containers to heat and/or store at temperatures above 120°F (49°C).

6 ADVERSE REACTIONS

The following adverse reactions are discussed in greater detail in other sections of the labeling:

- Effects on Endocrine System [see Warnings and Precautions (5.1)]
- Ophthalmic Adverse Reactions [see Warnings and Precautions (5.3)]

6.1 Clinical Trials Experience

Because clinical trials are conducted under widely varying conditions, adverse reaction rates observed in the clinical trials of a drug cannot be directly compared to rates in the clinical trials of another drug and may not reflect the rates observed in clinical practice.

In controlled clinical trials involving 821 subjects exposed to clobetasol propionate emulsion foam and vehicle foam, the pooled incidence of local adverse reactions in trials for atopic dermatitis and psoriasis with clobetasol propionate emulsion foam was 1.9% for application site atrophy and 1.6% for application site reaction. Most local adverse events were rated as mild to moderate and they were not affected by age, race, or gender.

6.2 Postmarketing Experience

Because these reactions are reported voluntarily from a population of uncertain size, it is not always possible to reliably estimate their frequency or establish a causal relationship to drug exposure.

The following adverse reactions have been identified during post-approval use of clobetasol formulations: erythema, pruritus, burning, alopecia, and dryness.

The following additional local adverse reactions have been reported with topical corticosteroids: folliculitis, acneiform eruptions, hypopigmentation, perioral dermatitis, allergic contact dermatitis, secondary infection, irritation, striae, and miliaria. They may occur more frequently with the use of occlusive dressings and higher potency corticosteroids, such as clobetasol propionate.

Cushing’s syndrome has been reported in infants and adults as a result of prolonged use of topical clobetasol propionate formulations.

Ophthalmic adverse reactions may include cataracts, glaucoma, increased intraocular pressure, and central serous chorioretinopathy.

8 USE IN SPECIFIC POPULATIONS

8.1 Pregnancy

Risk Summary

There are no available data on clobetasol propionate emulsion foam use in pregnant women to inform of a drug associated risk for adverse developmental outcomes.

Published data report a significantly increased risk of low birthweight with the use of greater than 300 grams of potent or very potent topical corticosteroid during a pregnancy. Advise pregnant women of the potential risk to a fetus and to use clobetasol propionate emulsion foam on the smallest area of skin and for the shortest duration possible (see Data).

In animal reproduction studies, increased malformations, such as cleft palate and skeletal abnormalities, were observed after subcutaneous administration of clobetasol propionate to pregnant mice and rabbits. No comparison of animal exposure with human exposure was computed.

The background risk of major birth defects and miscarriage for the indicated population is unknown. All pregnancies have a background risk of birth defect, loss, or other adverse outcomes. In the U.S. general population, the estimated background risk of major birth defects and miscarriage in clinically recognized pregnancies is 2 to 4% and 15 to 20%, respectively.

Data

Human Data

Multiple observational studies found no significant associations between maternal use of topical corticosteroids of any potency and congenital malformations, preterm delivery, or fetal mortality. However, when the dispensed amount of potent or very potent topical corticosteroid exceeded 300 g during the entire pregnancy, use was associated with an increase in low birth weight infants (adjusted RR, 7.74 [95% CI, 1.49 to 40.11]). In addition, a small cohort study, in which 28 sub-Saharan women using potent topical corticosteroids (27/28 used clobetasol propionate 0.05%) for skin lightening during pregnancy, noted a higher incidence of low birth weight infants in the exposed group. The majority of exposed subjects treated large areas of the body (a mean quantity of 60 g/month [range, 12 to 170 g]) over long periods of time.

Animal Data

Embryofetal development studies conducted with clobetasol propionate in mice using the subcutaneous route resulted in fetotoxicity at the highest dose tested (1 mg/kg) and malformations at all dose levels tested down to 0.03 mg/kg. Malformations seen included cleft palate and skeletal abnormalities.

In an embryofetal development study in rabbits, subcutaneous administration of clobetasol propionate resulted in malformations at doses of 0.003 and 0.01 mg/kg. Malformations seen included cleft palate, cranioschisis, and other skeletal abnormalities.

8.2 Lactation

Risk Summary

There is no information regarding the presence of clobetasol propionate in breast milk or its effects on the breastfed infant or on milk production. Systemically administered corticosteroids appear in human milk and could suppress growth, interfere with endogenous corticosteroid production, or cause other untoward effects. It is not known whether topical administration of clobetasol propionate could result in sufficient systemic absorption to produce detectable quantities in human milk. The developmental and health benefits of breastfeeding should be considered along with the mother’s clinical need for clobetasol propionate emulsion foam and any potential adverse effects on the breastfed infant from clobetasol propionate emulsion foam or from the underlying maternal condition.

Clinical Considerations

To minimize potential exposure to the breastfed infant via breast milk, use clobetasol propionate emulsion foam on the smallest area of skin and for the shortest duration possible while breastfeeding. Advise breastfeeding women not to apply clobetasol propionate emulsion foam directly to the nipple and areola to avoid direct infant exposure.

8.4 Pediatric Use

Use in pediatric patients younger than 12 years is not recommended because of the risk of HPA axis suppression.

After two weeks of twice-daily treatment with clobetasol propionate emulsion foam, 7 of 15 subjects (47%) aged 6 to 11 years demonstrated HPA axis suppression. The laboratory suppression was transient; in all subjects serum cortisol levels returned to normal when tested 4 weeks post-treatment.

In 92 subjects aged 12 to 17 years, safety was similar to that observed in the adult population. Based on these data, no adjustment of dosage of clobetasol propionate emulsion foam in adolescent patients aged 12 to 17 years is warranted [see Warnings and Precautions (5.1)].

Because of a higher ratio of skin surface area to body mass, pediatric patients are at a greater risk than adults of HPA axis suppression and Cushing’s syndrome when they are treated with topical corticosteroids. They are therefore also at greater risk of adrenal insufficiency during and/or after withdrawal of treatment.

HPA axis suppression, Cushing’s syndrome, linear growth retardation, delayed weight gain, and intracranial hypertension have been reported in children receiving topical corticosteroids. Manifestations of adrenal suppression in children include low plasma cortisol levels and an absence of response to ACTH stimulation. Manifestations of intracranial hypertension include bulging fontanelles (in infants), headaches, and bilateral papilledema. Administration of topical corticosteroids to children should be limited to the least amount compatible with an effective therapeutic regimen. Chronic corticosteroid therapy may interfere with the growth and development of children.

Adverse effects, including striae, have been reported with inappropriate use of topical corticosteroids in infants and children.

8.5 Geriatric Use

A limited number of subjects aged 65 years or older have been treated with clobetasol propionate emulsion foam (n = 58) in U.S. clinical trials. While the number of subjects is too small to permit separate analysis of efficacy and safety, the adverse reactions reported in this population were similar to those reported by younger subjects. Based on available data, no adjustment of dosage of clobetasol propionate emulsion foam in geriatric patients is warranted.

10 OVERDOSAGE

Topically applied clobetasol propionate emulsion foam can be absorbed in sufficient amounts to produce systemic effects.

11 DESCRIPTION

Clobetasol Propionate Emulsion Foam, 0.05% is a white to off-white emulsion aerosol foam containing the active ingredient clobetasol propionate, USP, a synthetic corticosteroid for topical dermatologic use. Clobetasol, an analog of prednisolone, has a high degree of glucocorticoid activity and a slight degree of mineralocorticoid activity.

Clobetasol propionate, USP is 21-chloro-9-fluoro-11β,17-dihydroxy-16β-methylpregna-1,4-diene-3,20-dione 17-propionate, with the empirical formula C25H32ClFO5, and a molecular weight of 467 g/mol.

The following is the chemical structure:

Clobetasol Propionate, USP

Clobetasol propionate, USP is a white to almost white crystalline powder, practically insoluble in water, slightly soluble in benzene and diethyl ether; sparingly soluble in ethanol; freely soluble in acetone, in dimethylsulfoxide, in chloroform, in methanol and in dioxane.

Each gram of Clobetasol Propionate Emulsion Foam, 0.05% contains 0.5 mg clobetasol propionate, USP. The foam also contains anhydrous citric acid, cetyl alcohol, cyclomethicone, isopropyl myristate, light mineral oil, polyoxyl-20 cetostearyl ether, potassium citrate, propylene glycol, purified water, sorbitan monolaurate, white petrolatum, and phenoxyethanol as a preservative.

Clobetasol Propionate Emulsion Foam is dispensed from an aluminum can pressurized with a hydrocarbon (propane/butane) propellant.

12 CLINICAL PHARMACOLOGY

12.1 Mechanism of Action

Corticosteroids play a role in cellular signaling, immune function, inflammation, and protein regulation; however, the precise mechanism of action in corticosteroid-responsive dermatoses is unknown.

12.2 Pharmacodynamics

In a trial evaluating the potential for HPA axis suppression using the cosyntropin stimulation test, clobetasol propionate emulsion foam demonstrated reversible adrenal suppression after two weeks of twice-daily use in subjects with atopic dermatitis of at least 30% body surface area (BSA). The proportion of subjects aged 12 years and older demonstrating HPA axis suppression was 16.2% (6 out of 37). In this trial HPA axis suppression was defined as serum cortisol level ≤18 mcg/dL 30 minutes post cosyntropin stimulation. The laboratory suppression was transient; in all subjects serum cortisol levels returned to normal when tested 4 weeks post treatment [see Warnings and Precautions (5.1), Use in Specific Populations (8.4)].

12.3 Pharmacokinetics

Topical corticosteroids can be absorbed from intact healthy skin. The extent of percutaneous absorption of topical corticosteroids is determined by many factors, including the product formulation and the integrity of the epidermal barrier. Occlusion, inflammation, and/or other disease processes in the skin may increase percutaneous absorption. The use of pharmacodynamic endpoints for assessing the systemic exposure of topical corticosteroids may be necessary due to the fact that circulating levels are often below the level of detection. Once absorbed through the skin, topical corticosteroids are metabolized primarily in the liver and are then excreted by the kidneys. Some corticosteroids and their metabolites are also excreted in the bile.

Following twice-daily application of clobetasol propionate emulsion foam for one week to 32 adult subjects with mild to moderate plaque-type psoriasis, mean peak plasma concentrations (±SD) of 59 ± 36 pg/mL of clobetasol were observed at around 5 hours post dose on Day 8.

13 NONCLINICAL TOXICOLOGY

13.1 Carcinogenesis, Mutagenesis, Impairment of Fertility

Long-term animal studies have not been performed to evaluate the carcinogenic potential of clobetasol propionate emulsion foam or clobetasol propionate.

In a 90-day repeat-dose toxicity study in rats, topical administration of clobetasol propionate emulsion foam at dose concentrations from 0.001% to 0.1% or from 0.03 to 0.3 mg/kg/day of clobetasol propionate resulted in a toxicity profile consistent with long term exposure to corticosteroids including adrenal atrophy, histopathological changes in several organ systems indicative of severe immune suppression and opportunistic fungal and bacterial infections. A no observable adverse effect level could not be determined in this study. Although the clinical relevance of the findings in animals to humans is not clear, sustained glucocorticoid-related immune suppression may increase the risk of infection and possibly the risk for carcinogenesis.

Clobetasol propionate was non-mutagenic in the Ames test, the mouse lymphoma test, the Saccharomyces cerevisiae gene conversion assay, and the E. coli B WP2 fluctuation test. In the in vivo mouse micronucleus test, a positive finding was observed at 24 hours, but not at 48 hours, following oral administration at a dose of 2,000 mg/kg.

Studies in the rat following subcutaneous administration of clobetasol propionate at dosage levels up to 0.05 mg/kg per day revealed that the females exhibited an increase in the number of resorbed embryos and a decrease in the number of living fetuses at the highest dose.

14 CLINICAL STUDIES

In a randomized trial of subjects 12 years and older with moderate to severe atopic dermatitis, 251 subjects were treated with clobetasol propionate emulsion foam and 126 subjects were treated with vehicle foam. Subjects were treated twice daily for 2 weeks. At the end of treatment, 131 of 251 subjects (52%) treated with clobetasol propionate emulsion foam compared with 18 of 126 subjects (14%) treated with vehicle foam achieved treatment success. Treatment success was defined by an Investigator’s Static Global Assessment (ISGA) score of clear (0) or almost clear (1) with at least 2 grades improvement from baseline, and scores of absent or minimal (0 or 1) for erythema and induration/papulation.
In an additional randomized trial of subjects 12 years and older with mild to moderate plaque-type psoriasis, 253 subjects were treated with clobetasol propionate emulsion foam and 123 subjects were treated with vehicle foam. Subjects were treated twice daily for 2 weeks. At the end of treatment, 41 of 253 subjects (16%) treated with clobetasol propionate emulsion foam compared with 5 of 123 subjects (4%) treated with vehicle foam achieved treatment success. Treatment success was defined by an ISGA score of clear (0) or almost clear (1) with at least 2 grades improvement from baseline, scores of none or faint/minimal (0 or 1) for erythema and scaling, and a score of none (0) for plaque thickness.

16 HOW SUPPLIED/STORAGE AND HANDLING

16.1 How Supplied

Clobetasol Propionate Emulsion Foam, 0.05% contains 0.5 mg of clobetasol propionate, USP per gram. The white to off-white emulsion aerosol foam is available as follows

- 50 g aluminum can NDC 68462-625-27
- 100 g aluminum can NDC 68462-625-94

16.2 Storage and Handling

Store at 20°C to 25°C (68°F to 77°F); excursions permitted to 15°C to 30°C (59°F to 86°F) [see USP Controlled Room Temperature].

FLAMMABLE. AVOID FIRE, FLAME OR SMOKING DURING AND IMMEDIATELY FOLLOWING APPLICATION.

Contents under pressure. Do not puncture or incinerate. Do not expose to heat or store at temperatures above 120°F (49°C).

Keep out of reach of children.

17 PATIENT COUNSELING INFORMATION

See FDA-Approved Patient Labeling (Patient Information)

Effects on Endocrine System

Clobetasol propionate emulsion foam may cause HPA axis suppression. Advise patients that use of topical corticosteroids, including clobetasol propionate emulsion foam, may require periodic evaluation for HPA axis suppression. Topical corticosteroids may have other endocrine effects. Concomitant use of multiple corticosteroid-containing products may increase the total systemic exposure to topical corticosteroids. Patients should inform their physician(s) that they are using clobetasol propionate emulsion foam if surgery is contemplated [see Warnings and Precautions (5.1)].

Ophthalmic Adverse Reactions

Advise patients to report any visual symptoms to their healthcare providers [see Warnings and Precautions (5.3)].

Local Adverse Reactions

Report any signs of local adverse reactions to the physician. Advise patients that local reactions and skin atrophy are more likely to occur with occlusive use or prolonged use [see Warnings and Precautions (5.2)].

Pregnancy

Advise a pregnant woman that use of clobetasol propionate emulsion foam may cause fetal harm and to use clobetasol propionate emulsion foam on the smallest area of skin and for the shortest duration possible [see Use in Specific Populations (8.1)].

Lactation

Advise a woman to use clobetasol propionate emulsion foam on the smallest area of skin and for the shortest duration possible while breastfeeding. Advise breastfeeding women not to apply clobetasol propionate emulsion foam directly to the nipple and areola to avoid direct infant exposure [see Use in Specific Populations (8.2)].

Important Administration Instructions

Patients using topical corticosteroids should receive the following information and instructions:

- This medication is to be used as directed by the physician. It is for external use only. Unless directed by the prescriber, it should not be used on the face or in skin-fold areas, such as the underarms or groin. Avoid contact with the eyes or other mucous membranes. Wash hands after use.
- As with other corticosteroids, therapy should be discontinued when control is achieved. If no improvement is seen within 2 weeks, contact the physician.
- Do not use for more than 50 grams per week of clobetasol propionate emulsion foam, or an amount greater than 21 capfuls per week [see Dosage and Administration (2)].
- This medication is flammable; avoid heat, flame, or smoking when applying this product.
For additional information, call Glenmark Pharmaceuticals Inc., USA at 1 (888) 721-7115.

Distributed by:

Glenmark Pharmaceuticals Inc., USA

Elmwood Park, NJ 07407

Questions? 1 (888) 721-7115

www.glenmarkpharma-us.com

August 2025

PATIENT INFORMATION

Clobetasol Propionate

(kloe bay’ ta sol proe’ pee oh nate) Foam

Important: For skin use only. Do not get clobetasol propionate emulsion foam in your eyes, mouth, or vagina.

What is clobetasol propionate emulsion foam?

Clobetasol propionate emulsion foam is a prescription corticosteroid medicine used on the skin (topical) to treat people 12 years of age and older with certain skin conditions that cause red, flaky, and itchy skin.

Clobetasol propionate emulsion foam is not recommended for use in children under 12 years of age.

Clobetasol propionate emulsion foam should not be used:

- on your face, underarms, or groin area
- if you have skin thinning (atrophy) at the treatment area

You should not use clobetasol propionate emulsion foam for longer than 2 weeks in a row.

You should not use more than 50 grams or 21 capfuls of clobetasol propionate emulsion foam in 1 week.

Before using clobetasol propionate emulsion foam, tell your healthcare provider about all of your medical conditions, including if you:

- have had irritation or other skin reaction to a steroid medicine in the past.
- have a skin infection. You may need medicine to treat the skin infection before using clobetasol propionate emulsion foam.
- have diabetes.
- have adrenal gland problems.
- have liver problems.
- plan to have surgery.
- are pregnant or plan to become pregnant. It is not known if clobetasol propionate emulsion foam will harm your unborn baby. If you use clobetasol propionate emulsion foam during pregnancy, use clobetasol propionate emulsion foam on the smallest area of skin and for the shortest time needed.
- are breastfeeding or plan to breastfeed. It is not known if clobetasol propionate passes into your breast milk. If you use clobetasol propionate emulsion foam while breastfeeding, use clobetasol propionate emulsion foam on the smallest area of skin and for the shortest time needed. Do not apply clobetasol propionate emulsion foam directly to the nipple and areola to avoid getting clobetasol propionate emulsion foam into your baby’s mouth.

Tell your healthcare provider about all the medicine you take including prescription and over-the‑counter medicines, vitamins, and herbal supplements. Do not use other products containing a corticosteroid medicine during treatment with clobetasol propionate emulsion foam without talking to your healthcare provider first.

How should I use clobetasol propionate emulsion foam?

See the“Instructions for Use” for detailed information about the right way to apply clobetasol propionate emulsion foam.

- Use clobetasol propionate emulsion foam exactly as your healthcare provider tells you to use it.
- Apply a thin layer of clobetasol propionate emulsion foam to the affected area 2 times each day, 1 time in the morning and 1 time at night, or as directed by your healthcare provider.
- Do not bandage, wrap or cover your treated area unless your healthcare provider tells you to.
- Talk to your healthcare provider if your skin does not improve after 2 weeks of treatment with clobetasol propionate emulsion foam.
- Wash your hands after using clobetasol propionate emulsion foam.

What should I avoid while using clobetasol propionate emulsion foam?

Clobetasol propionate emulsion foam is flammable. Avoid heat, flame, or smoking during and right after you apply clobetasol propionate emulsion foam to your skin.

What are the possible side effects of clobetasol propionate emulsion foam?

Clobetasol propionate emulsion foam may cause serious side effects, including:

- Clobetasol propionate emulsion foam can pass through your skin. Too much clobetasol propionate emulsion foam passing through your skin can cause adrenal glands to stop working.
- Cushing’s syndrome, a condition that happens when the body is exposed to too much of the hormone cortisol.
- High blood sugar (hyperglycemia)
- Vision problems. Clobetasol propionate emulsion foam may increase your chance of developing vision problems such as cataract(s) and glaucoma. Tell your healthcare provider if you develop blurred vision or other vision problems during your treatment with clobetasol propionate emulsion foam.
- Skin reactions at the treated site. Tell your healthcare provider if you get any skin reactions or skin infections.
- Effects on growth and weight in children.

Your healthcare provider may do certain blood tests to check for side effects.

The most common side effects of clobetasol propionate emulsion foam include:

• thinning of skin • itching
  • burning • dryness
  • redness

These are not all the side effects of clobetasol propionate emulsion foam.

Call your healthcare provider for medical advice about side effects. You may report side effects to FDA at 1-800-FDA-1088.

How should I store clobetasol propionate emulsion foam?

- Store clobetasol propionate emulsion foam at room temperature between 68°F to 77°F (20°C to 25°C).
- Do not break through (puncture) clobetasol propionate emulsion foam can.
- Never throw the can into a fire, even if the can is empty.
- Do not store clobetasol propionate emulsion foam near heat or at temperatures above 120°F (49°C).

Keep clobetasol propionate emulsion foam and all medicines out of the reach of children.

General information about the safe and effective use of clobetasol propionate emulsion foam

Medicines are sometimes prescribed for purposes other than those listed in a Patient Information leaflet. Do not use clobetasol propionate emulsion foam for a condition for which it was not prescribed. Do not give clobetasol propionate emulsion foam to other people, even if they have the same condition that you have. It may harm them. You can ask your healthcare provider or pharmacist for information about clobetasol propionate emulsion foam that is written for health professionals.

What are the ingredients in clobetasol propionate emulsion foam?

Active ingredient: clobetasol propionate

Inactive ingredients: anhydrous citric acid, cetyl alcohol, cyclomethicone, isopropyl myristate, light mineral oil, polyoxyl-20 cetostearyl ether, potassium citrate, propylene glycol, purified water, sorbitan monolaurate, white petrolatum, and phenoxyethanol as a preservative; pressurized with a hydrocarbon (propane/butane) propellant.

Distributed by:

Glenmark Pharmaceuticals Inc., USA

Elmwood Park, NJ 07407

Questions? 1 (888) 721-7115

www.glenmarkpharma-us.com

August 2025

This Patient Information has been approved by the U.S. Food and Drug Administration.

INSTRUCTIONS FOR USE

Clobetasol Propionate

(kloe bay’ ta sol proe’ pee oh nate) Foam

Important information: Clobetasol propionate emulsion foam is for use on the skin only. Do not get clobetasol propionate emulsion foam in your eyes, mouth, or vagina; if contact happens, rinse well with water.

How to apply clobetasol propionate emulsion foam

Figure A

Step 1: Before applying clobetasol propionate emulsion foam for the first time, break the tiny plastic piece at the base of the can's rim by gently pushing back (away from the piece) on the nozzle. (See Figure A).

Figure B

Step 2: Shake the can of clobetasol propionate emulsion foam before use. (See Figure B).

Figure C

Step 3: Turn the can of clobetasol propionate emulsion foam upside down and press the nozzle. See Figure C.

Figure D

Step 4: Press down on the actuator to dispense a small amount of clobetasol propionate emulsion foam into the palm of your hand. (See Figure D).

Figure E

Step 5: Apply a thin layer of clobetasol propionate emulsion foam to cover the affected area. Gently rub the foam into the affected area until the foam disappears. (See Figure E).

Step 6: Wash your hands after applying clobetasol propionate emulsion foam.

- Throw away any of the unused medicine that you dispensed out of the can.

This Instructions for Use has been approved by the U.S. Food and Drug Administration.

Distributed by:

Glenmark Pharmaceuticals Inc., USA

Elmwood Park, NJ 07407

Questions? 1 (888) 721-7115

www.glenmarkpharma-us.com

August 2025